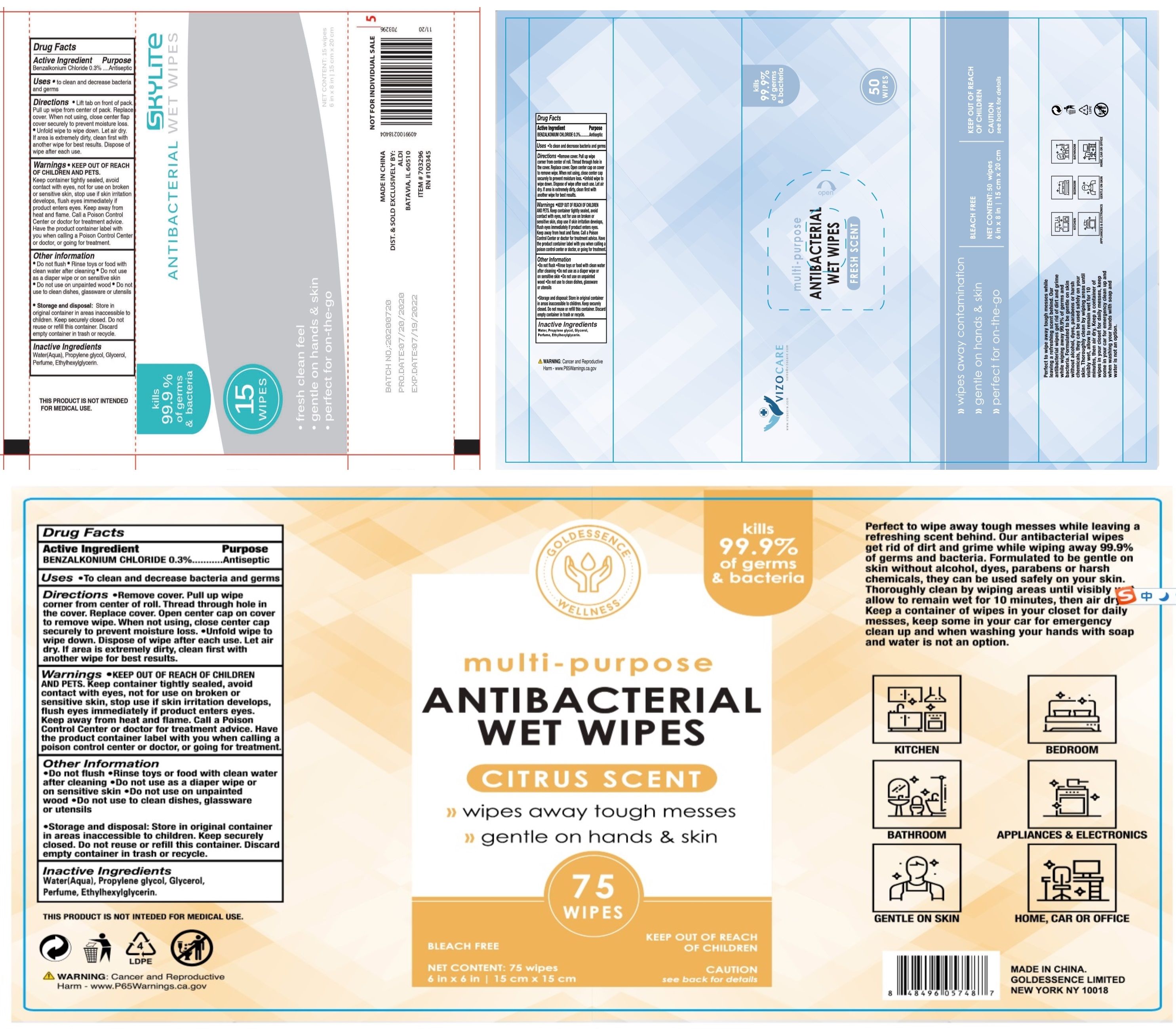 DRUG LABEL: ANTIBACTERIAL WET WIPES
NDC: 79805-002 | Form: CLOTH
Manufacturer: JUXIN (Jiangsu) New Material Packaging Co., Ltd.
Category: otc | Type: HUMAN OTC DRUG LABEL
Date: 20250103

ACTIVE INGREDIENTS: BENZALKONIUM CHLORIDE 0.3 g/100 1
INACTIVE INGREDIENTS: PROPYLENE GLYCOL; GLYCERIN; WATER; CANANGA ODORATA FLOWER; ETHYLHEXYLGLYCERIN

79805-002 ANTIBACTERIAL WET WIPES

Active Ingredient(s)

Benzalkonium Chloride 0.3%

Purpose

Antiseptic

Use

to clean and decrease bacteriaand germs

Warnings

Keep container tightly sealed, avoid contact with eyes, not for use on broken or sensitive skin, stop use if skin irritation develops, flush eyes immediately if product enters eyes. Keep away from heat and flame. Call a Poison Control Center or doctor for treatment advice.
Have the product container label with you when calling a Poison Control Center or doctor, or going for treatment

Do not use as a diaper wipe or on sensitive skin
Do not use on unpainted wood
Do not use to clean dishes, glassware or utensils

WHEN USING

Do not flush. Rinse toys or food with clean water after cleaning.

STOP USE

/

KEEP OUT OF REACH OF CHILDREN AND PETS

Directions

Lift tab on front of pack.
Pull up wipe from center of pack. Replace cover. When not using, close center flap cover securely to prevent moisture losse.
Unfold wipe to wipe down. Let air dry.
If area is extremely dirty, clean first with another wipe for best results. Dispose of wipe after each use

Other information

Storage and disposal: Store in original container in areas inaccessible to children. Keep securely closed. Do not reuse or refill this container. Discard empty container in trash or recycle

Inactive ingredients

Water(Aqua), Propylene glycol, Glycerol,Perfume, Ethylhexylglycerin